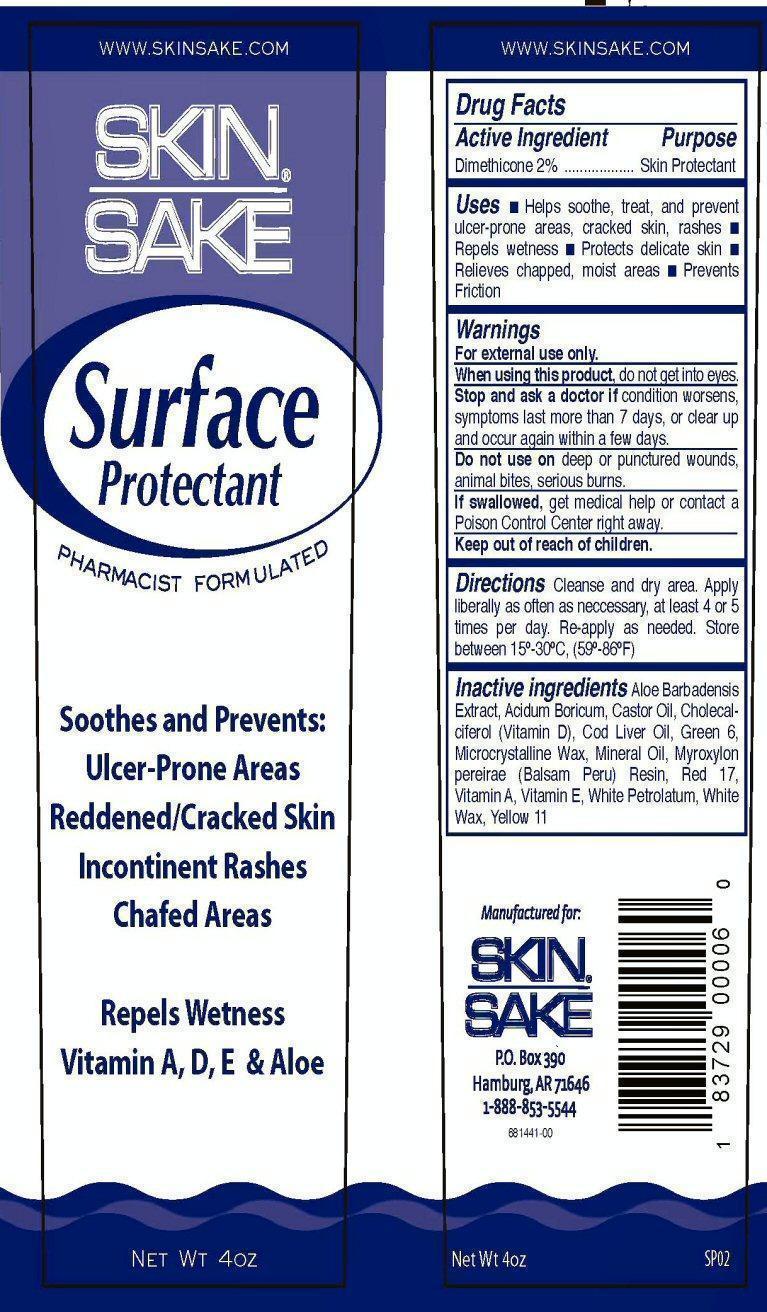 DRUG LABEL: SKIN SAKE Surface Protectant
NDC: 43447-4410 | Form: OINTMENT
Manufacturer: Skin Sake, LLC
Category: otc | Type: HUMAN OTC DRUG LABEL
Date: 20130424

ACTIVE INGREDIENTS: DIMETHICONE 2.272 g/113.6 g
INACTIVE INGREDIENTS: ALOE VERA LEAF; BORIC ACID; CASTOR OIL; CHOLECALCIFEROL; COD LIVER OIL; D&C GREEN NO. 6; MICROCRYSTALLINE WAX; MINERAL OIL; BALSAM PERU; D&C RED NO. 17; VITAMIN A; .ALPHA.-TOCOPHEROL; PETROLATUM; WHITE WAX; D&C YELLOW NO. 11

Active Ingredient

Drug Facts

Active Ingredient

Dimethicone 2%

Purpose

Skin Protectant

Keep out of reach of children

Uses

- Helps soothe, treat, and prevent ulcer-prone areas, cracked skin, rashes
- Repels wetness
- Protects delicate skin
- Relieves chapped, moist areas
- Prevents friction

Warnings

For external use only.

When using this product, do not get into eyes.

Stop and ask a doctor if condition worsens, symptoms last more than 7 days, or clear up and occur again within a few days.

Do not use on deep or punctured wounds, animal bites, serious burns.

If swallowed, get medical help or contact a Poison Control Center right away.

Directions

Cleanse and dry area. Apply liberally as often as necessary, at least 4 or 5 times per day. Re-apply as needed.

Store between 15° -30° C, (59° -86° F)

Inactive ingredients

Aloe Barbadensis Extract, Acidium Boricum, Castor Oil, Cholecalciferol (Vitamin D), Cod Liver Oil, Green 6, Microcrystalline Wax, Mineral Oil, Myroxylon pereirae (Balsam Peru) Resin, Red 17, Vitamin A, Vitamin E, White Petrolatum, White Wax, Yellow 11

Product Label

www.skinsake.com

SKIN SAKE

Surface Protectant

PHARMACIST FORMULATED

Soothes and Prevents:

Ulcer-Prone Areas
Reddened/Cracked Skin
Incontinent Rashes
Chafed Areas

Repels Wetness
Vitamin A, D, E, and Aloe

NET WT 4OZ SP02

Manufactured for:

Skin Sake

P.O. Box 390

Hamburg, AR 71646

1-888-853-5544

681441-00